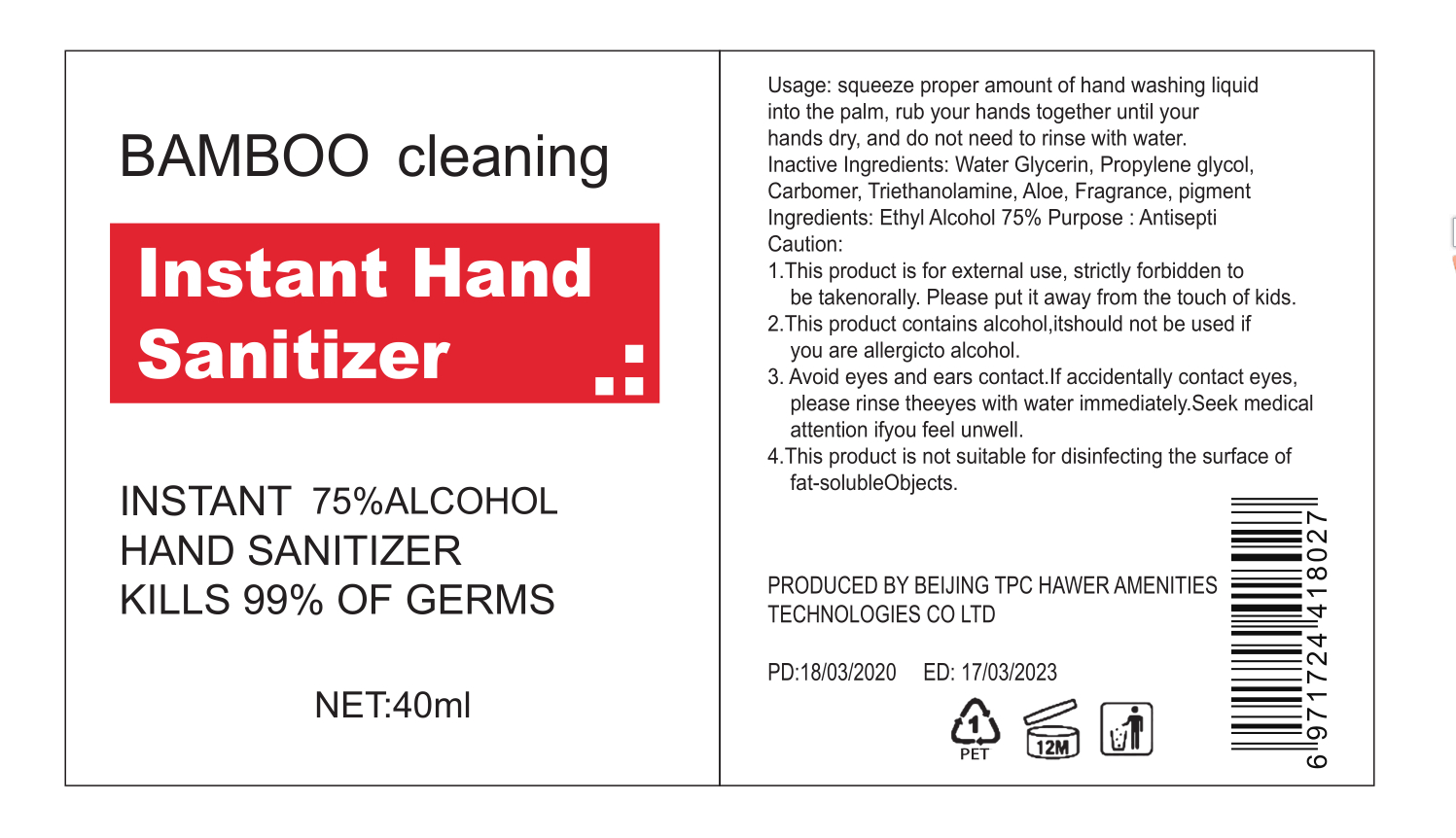 DRUG LABEL: bamboo Instand Hand Sanitizer
NDC: 41254-002 | Form: LIQUID
Manufacturer: Jiangsu Hawer Amenities Technology Co.,Ltd
Category: otc | Type: HUMAN OTC DRUG LABEL
Date: 20200413

ACTIVE INGREDIENTS: ALCOHOL 30 mL/40 mL
INACTIVE INGREDIENTS: AMINOMETHYLPROPANOL; WATER; GLYCERIN; CARBOMER HOMOPOLYMER, UNSPECIFIED TYPE

INACTIVE INGREDIENT

Water Glycerin, Propylene glycol,Carbomer, Triethanolamine, Aloe, Fragrance, pigment

ACTIVE INGREDIENT

Ethyl Alcohol

keep out of reach of children

INDICATIONS AND USAGE

Squeeze proper amount of hand washing liquid into the palm, rub your hands together until your
hands dry, and do not need to rinse with water.

PURPOSE

Disinfection
Sterilization
No Rinseing

DOSAGE AND ADMINISTRATION

This product is for external use, strictly forbidden to be takenorally. Please put it away from the touch of kids.

WARNINGS

This product contains alcohol,it should not be used if you are allergicto alcohol.
Avoid eyes and ears contact.lf accidentally contact eyes, please rinse the eyes with water immediately.

Seek medical attention if you feel unwell.
This product is not suitable for disinfecting the surface of fat-solubleObjects.